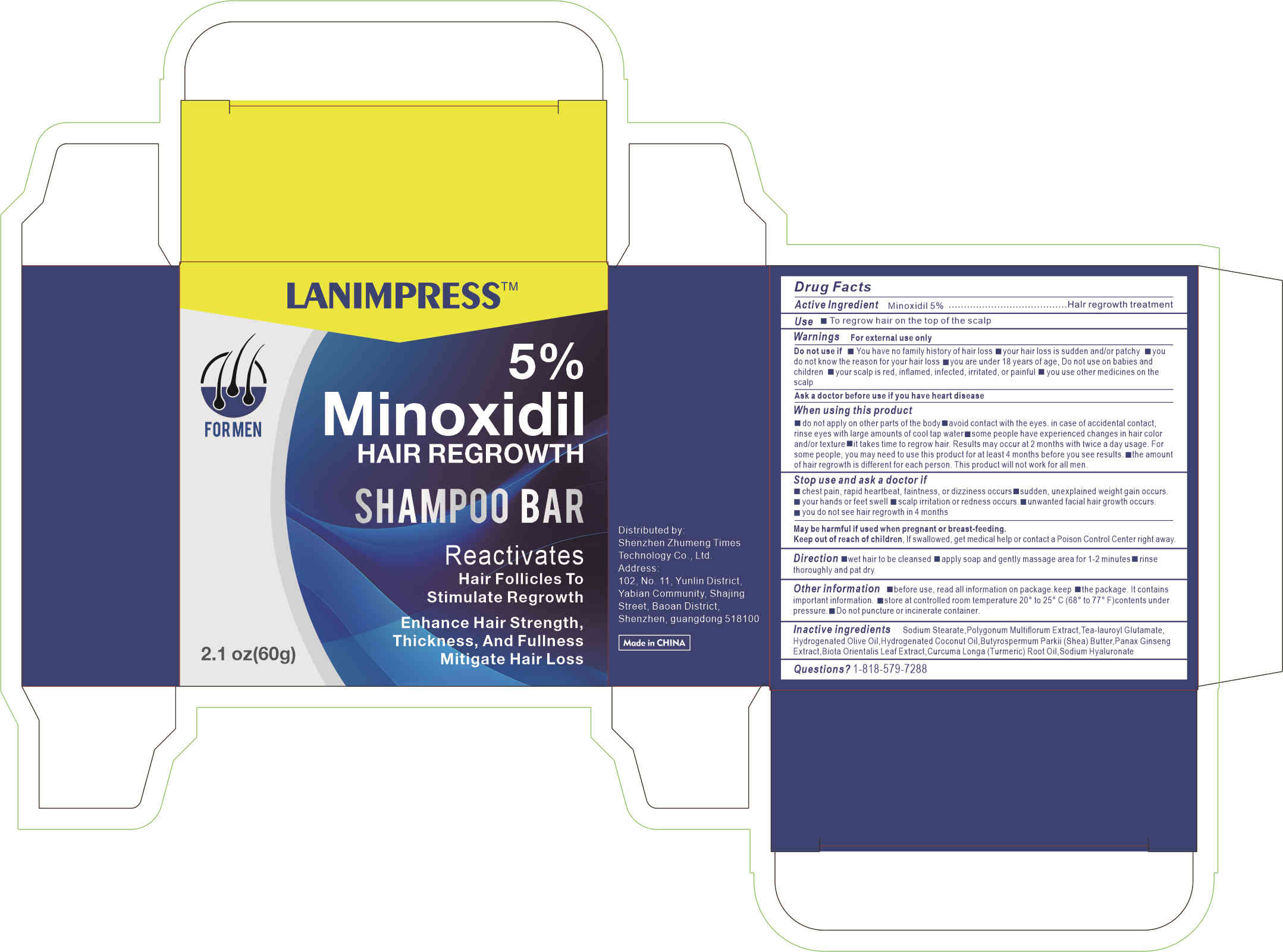 DRUG LABEL: 5%Minoxidil HAIR REGROWTH
NDC: 84372-007 | Form: LIQUID
Manufacturer: Shenzhen Zhumeng Times Technology Co., Ltd.
Category: otc | Type: HUMAN OTC DRUG LABEL
Date: 20240820

ACTIVE INGREDIENTS: MINOXIDIL 5 g/100 g
INACTIVE INGREDIENTS: TRIETHANOLAMINE LAUROYL GLUTAMATE; PLATYCLADUS ORIENTALIS LEAF; SODIUM STEARATE; BUTYROSPERMUM PARKII (SHEA) BUTTER UNSAPONIFIABLES; HYALURONATE SODIUM; HYDROGENATED OLIVE OIL; ASIAN GINSENG; TURMERIC OIL; REYNOUTRIA MULTIFLORA ROOT

Active ingredients

Minoxidil 5%

Purpose

Halr regrowth treatment for men

Uses

wet hair to be cleansed

apply soap and gently massage area for 1-2 minutes

rinse thoroughly and pat dry

Warnings

For external use only

Do not use if

You have no famlly history of hair loss

your hair loss is sudden and/or patchy

you do not know the reason for your hair loss

you are under 18 years of age, Do not use on babies and children

your scalp is red, inflamed, infected, irritated, or painful

you use other medicines on the scalp

Ask a doctor before use if you have heart disease

Dosage and administration

For external use only.

Do not use

Stop use and ask a doctor if

chest pain, rapid heartbeat, faintness, or dizziness occurs

sudden, unexplained weight gain occurs

your hands or feet swell

scalp irritation or redness occurs

unwanted facial hair growth occurs

you do not see hair regrowth in 4 months

May be harmful if used when pregnant or breast-feeding.

Keep out of reach of children, lf swallowed, get medical help or contact a Poison Control Center right away.

When using section

do not apply on other parts of the body

avoid contact with the eyes. in case of accidental contact, rinse eyes with large amounts of cool tap water

some people have experienced changes in hair color and/or texture

it takes time to regrow hair. Results may occur at 2 months with twice a day usage. For some people, you may need to use this product for at least 4 months before you see results.

the amount of hair regrowth is different for each person. This product will notwork for all men.

stop use

on broken or irritated scalp

Keep out of reach of children.

If sxralowed, get medical help or contact a Poison Conirol Cenler ngiht away.

Inactive ingredients

Sodium stearate,POLYGONUM MULTIFLORUM EXTRACT,TEA-Lauroyl Glutamate,HYDROGENATED OLIVE OIL,HYDROGENATED COCONUT OIL,BUTYROSPERMUM PARKII (SHEA) BUTTER,PANAX GINSENG EXTRACT,BIOTA ORIENTALIS LEAF EXTRACT,Curcuma Longa (Turmeric) Root Oil,SODIUM HYALURONATE